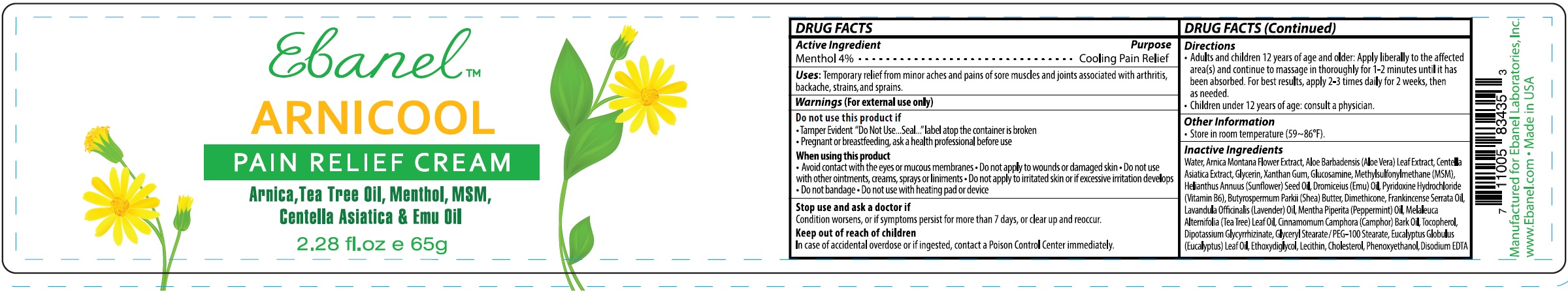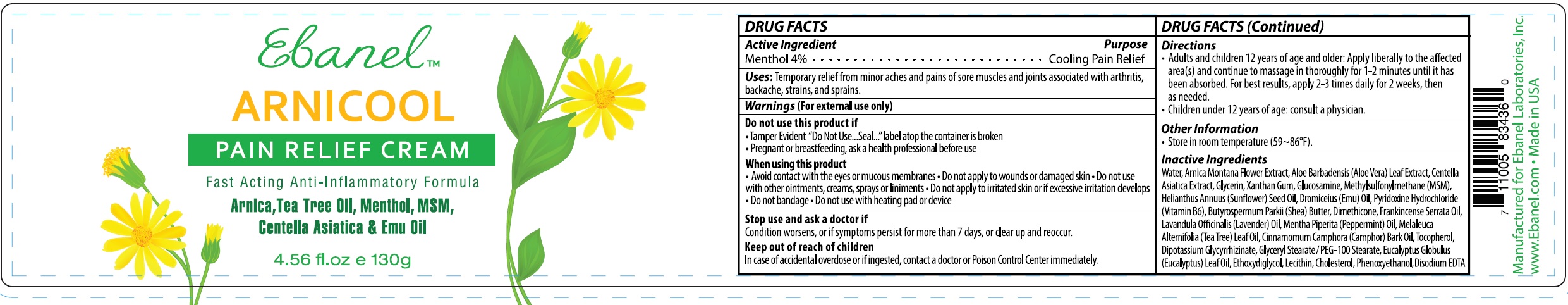 DRUG LABEL: ARNICOOL
NDC: 63742-007 | Form: CREAM
Manufacturer: Clinical Resolution Laboratory, Inc.
Category: otc | Type: HUMAN OTC DRUG LABEL
Date: 20231226

ACTIVE INGREDIENTS: MENTHOL 40 mg/1 g
INACTIVE INGREDIENTS: WATER; ARNICA MONTANA FLOWER; ALOE VERA LEAF; CENTELLA ASIATICA; GLYCERIN; XANTHAN GUM; GLUCOSAMINE; DIMETHYL SULFONE; HELIANTHUS ANNUUS FLOWERING TOP; EMU; PYRIDOXINE HYDROCHLORIDE; SHEA BUTTER; DIMETHICONE; LAVENDER OIL; PEPPERMINT OIL; TEA TREE OIL; CAMPHOR OIL; TOCOPHEROL; GLYCYRRHIZINATE DIPOTASSIUM; GLYCERYL MONOSTEARATE; EUCALYPTUS GUM; DIETHYLENE GLYCOL MONOETHYL ETHER; CHOLESTEROL; PHENOXYETHANOL; EDETATE DISODIUM ANHYDROUS

ARNICOOL

Active Ingredient

Menthol 4%

Purpose

Cooling Pain Relief

Uses

Temporary relief from minor aches and pains of sore muscles and joints associated with arthritis, backache, strains, and sprains.

Warnings

(For external use only)

Do not use this product if

- Tamper Evident "Do Not Use...Seal..."label atop the container is broken
- Pregnant or breastfeeding, ask a health professional before use

When using this product

- Avoid contact with the eyes or mucous membranes
- Do not apply to wounds or damaged skin
- Do not use with other ointments, creams, sprays or liniments
- Do not apply to irritated skin or if excessive irritation develops
- Do not bandage
- Do not use with heating pad or device

Stop use and ask a doctor if

Condition worsens, or if symptoms persist for more than 7 days, or clear up and reccur.

Keep out of reach of children

In case of accidental overdose or if ingested, contact a doctor or Poison Control Center immediately.

Directions

- Adults and children 12 years of age older: Apply liberally to the affected area(s) and continue to massage in thoroughly for 1-2 minutes until it has been absorbed. For best results, apply 2-3 times daily for 2 weeks, then as needed.
- Children under 12 years of age:consult a physician.

Other Information

- Store in room temperature (59~86°F).

Inactive Ingredients

Water, Arnica Montana Flower Extract, Aloe Barbadensis (Aloe Vera) Leaf Extract, Centella Asiatica Extract, Glycerin, Xanthan Gum, Glucosamine, Methylsulfonylmethane (MSM), Helianthus Annuus (Sunflower) Seed Oil, Dromiceius (Emu) Oil, Pyridoxine Hydrochloride (Vitamin B6), Butyrospermum Parkii (Shea) Butter, Dimethicone, Frankincense Serrata Oil, Lavandula Officinalis (Lavender) Oil, Mentha Piperita (Peppermint) Oil, Melaleuca Alternifolia (Tea Tree) Leaf Oil, Cinnamomum Camphora (Camphor) Bark Oil, Tocopherol, Dipotassium Glycyrrhizinate, Glyceryl Stearate / PEG-100 Stearate, Eucalyptus Globulus (Eucalyptus) Leaf Oil, Ethoxydiglycol, Lecithin, Cholesterol, Phenoxyethanol, Disodium EDTA